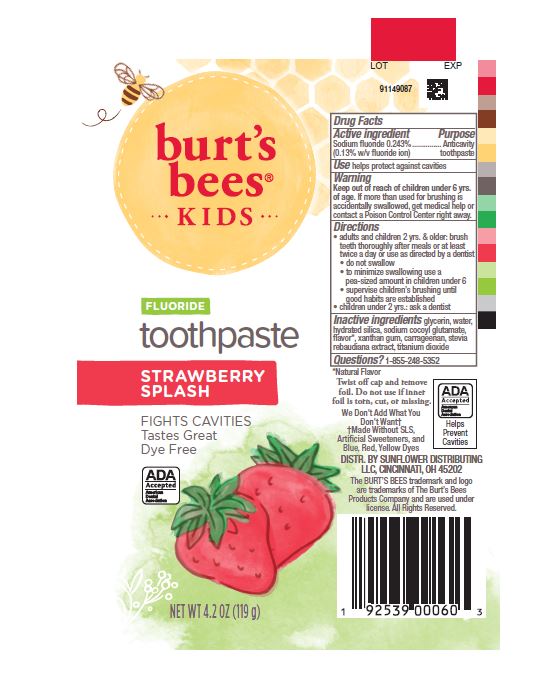 DRUG LABEL: Burts Bees
NDC: 37000-980 | Form: PASTE, DENTIFRICE
Manufacturer: Procter & Gamble Manufacturing Company
Category: otc | Type: HUMAN OTC DRUG LABEL
Date: 20250820

ACTIVE INGREDIENTS: SODIUM FLUORIDE 1.3 mg/1 g
INACTIVE INGREDIENTS: CARRAGEENAN; TITANIUM DIOXIDE; XANTHAN GUM; WATER; HYDRATED SILICA; GLYCERIN; STEVIA REBAUDIANA WHOLE; SODIUM COCOYL GLUTAMATE

Burt's Bees Kids Strawberry Splash

Drug Facts

Active ingredient

Sodium fluoride 0.243% (0.13% w/v fluoride ion)

Purpose

Anticavity toothpaste

Use

helps protect against cavities

Warnings

Keep out of reach of children under 6 yrs of age. If more than used for brushing is accidentally swallowed, get medical help or contact a Poison Control Center right away.

Directions

- adults and children 2 yrs. & older: brush teeth thoroughly after meals or at least twice a day or use as directed by a dentist
- do not swallow
- to minimize swallowing use a pea-sized amount in children under 6
- supervise children’s brushing until good habits are established
- children under 2 yrs.: ask a dentist

Inactive ingredients

glycerin, water, hydrated silica, sodium cocoyl glutamate, flavor*, xanthan gum, carrageenan, stevia rebaudiana extract, titanium dioxide

Questions?

1-855-248-5352

*Natural Flavor

DISTR. BY SUNFLOWER DISTRIBUTING
LLC, CINCINNATI, OH 45202

PRINCIPAL DISPLAY PANEL - 119 g tube

burt's

bees®

KIDS

FLUORIDE

toothpaste

STRARBERRY SPLASH

FIGHTS CAVITIES
Tastes Great
Dye Free

NET WT 4.2 OZ (119 g)